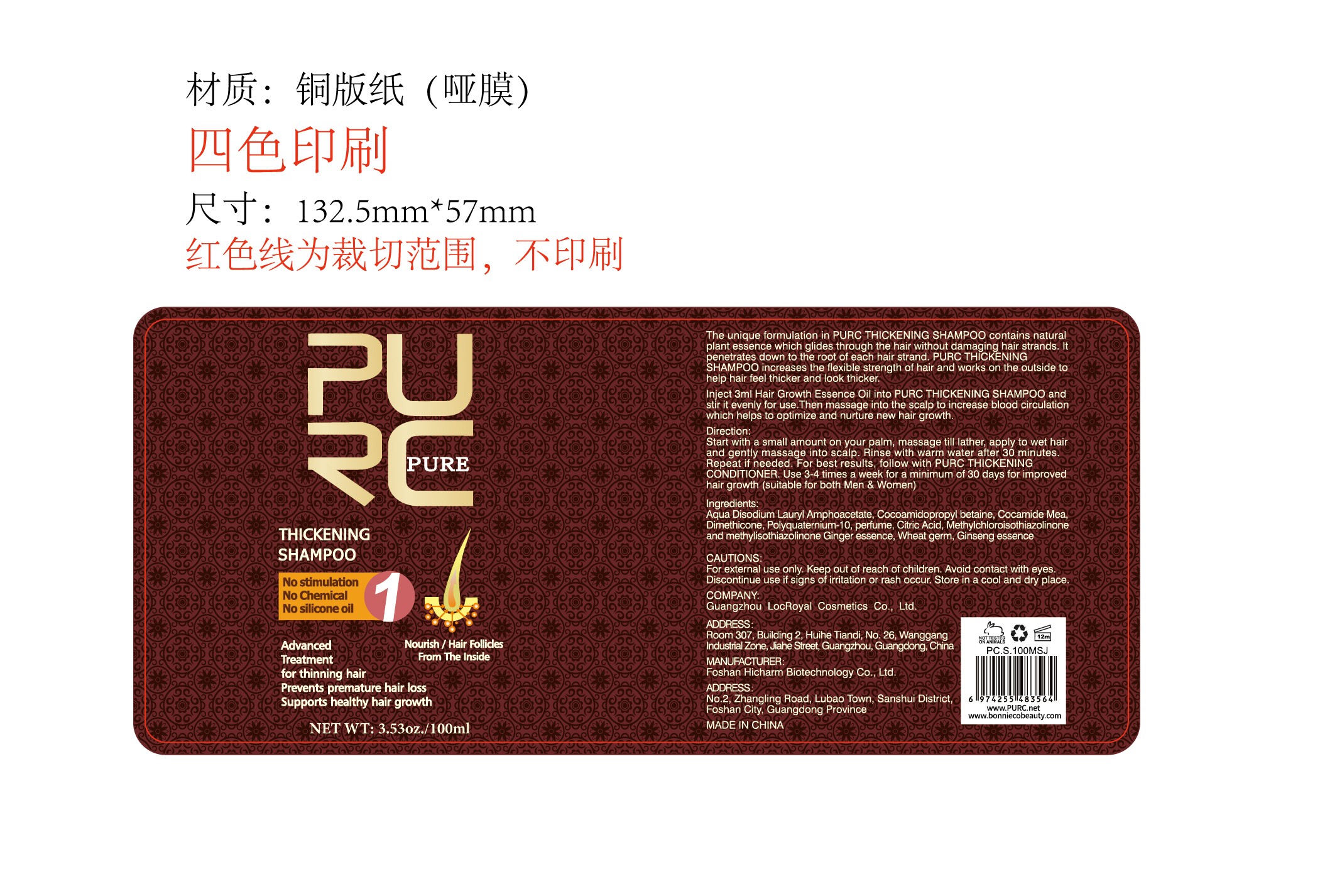 DRUG LABEL: Purc Thickening Shampoo.
NDC: 84186-019 | Form: SHAMPOO
Manufacturer: Guangzhou Bonnieco Cosmetics Co., Ltd
Category: otc | Type: HUMAN OTC DRUG LABEL
Date: 20240708

ACTIVE INGREDIENTS: DISODIUM LAURYL PHOSPHATE 5 g/100 mL
INACTIVE INGREDIENTS: ASIAN GINSENG; POLYQUATERNIUM-10 (10000 MPA.S AT 2%); DIMETHICONE 6; WHEAT GERM; METHYLCHLOROISOTHIAZOLINONE; COCAMIDOPROPYL BETAINE; COCO MONOETHANOLAMIDE; MELANOMA ANTIGEN PREFERENTIALLY EXPRESSED IN TUMORS; WATER; ACONITIC ACID

84186-019

Active Ingredient

Disodium Lauryl Amphoacetate 5%

Purpose

Advanced
Treatment
for thinning hair
Prevents premature hair loss
Supports healthy hair growth

Use

Inject 3ml Hair Growth Essence Oil into PURC THICKENING SHAMPOO and stir it evenly for use.Then massage into the scalp to increase blood circulation which helps to optimize and nurture new hair growth.

Warnings

For external use only. Keep out of reach of children. Avoid contact with eyes.
Discontinue use if signs of irritation or rash occur. Store in a cool and dry place.

Do not use

The unique formulation in PURC THICKENING SHAMPOO contains natural plant essence which glides through the hair without damaging hair strands. lt penetrates down to the root of each hair strand. PURC THICKENING

SHAMPOO increases the flexible strength of hair and works on the outside to help hair feel thicker and look thicker

When Using

In case of contact with the eyes, rinse immediately with plenty of water.

Stop Use

If discomfort arises, please immediately stop using the product and seek the assistance of a dermatologist.

Ask Doctor

If discomfort arises, please immediately stop using the product and seek the assistance of a dermatologist.

Keep Oot Of Reach Of Children

Directions

Start with a small amount on your palm, massage till lather, apply to wet hair
and gently massage into scalp. Rinse with warm water after 30 minutes.
Repeat if needed. For best results, follow with PURC THICKENING
CONDITIONER, Use 3-4 times a week for a minimum of 30 days for improved
hair growth (suitable for both Men & Women)

Inactive ingredients

Aqua Disodium Lauryl Amphoacetate, Cocoamidopropyl betaine, Cocamide Mea, Dimethicone, Polyquaternium-10, perume, Citric Acid, Methylchloroisothiazolinone and methylisothiazolinone Ginger essence, Wheat germ, Ginseng essence